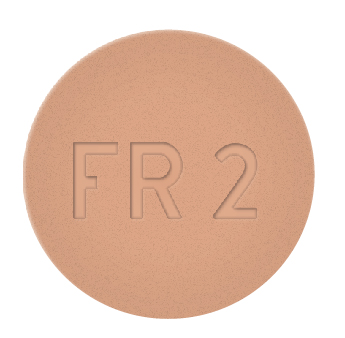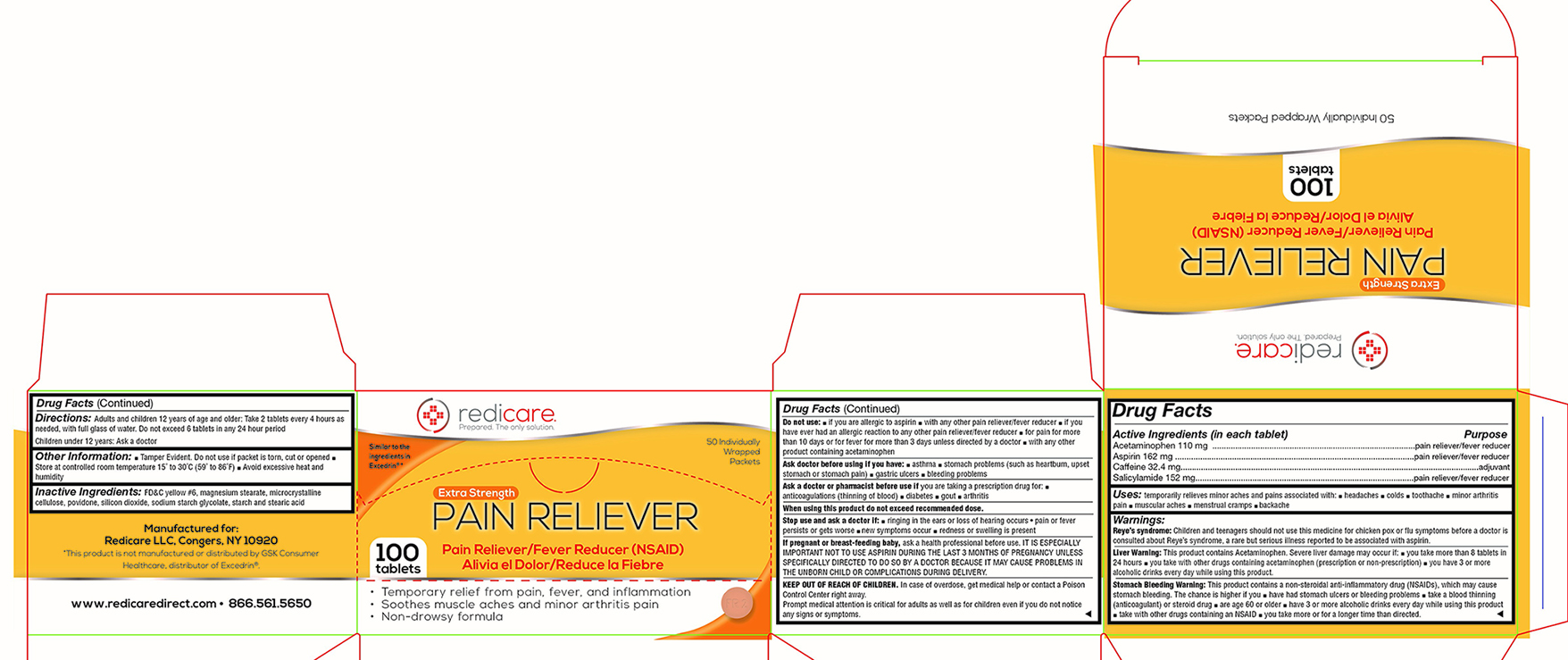 DRUG LABEL: Extra Strength Pain Reliever
NDC: 71105-242 | Form: TABLET
Manufacturer: Redicare LLC
Category: otc | Type: HUMAN OTC DRUG LABEL
Date: 20210702

ACTIVE INGREDIENTS: ASPIRIN 162 mg/1 1; ACETAMINOPHEN 110 mg/1 1; SALICYLAMIDE 152 mg/1 1; CAFFEINE 32.4 mg/1 1
INACTIVE INGREDIENTS: MAGNESIUM STEARATE; FD&C YELLOW NO. 6; CELLULOSE, MICROCRYSTALLINE; STARCH, CORN; STEARIC ACID

Pain Reliever

Active Ingredient

Acetaminophen 110 mg .....................................................................................pain reliever/fever reducer

Aspirin 162 mg .....................................................................................................pain reliever/fever reducer

Caffeine 32.4 mg...............................................................................................................................adjuvant

Salicylamide 152 mg............................................................................................pain reliever/fever reducer

Uses:

temporarily relieves minor aches and pains associated with ■ headaches ■ colds ■ a toothache ■ minor arthritis pain ■ muscular aches ■ menstrual cramps ■ a backache

Warnings: Reye’s syndrome:

Children and teenagers should not use this medicine for chicken pox or flu symptoms before a doctor is consulted about Reye’s syndrome, a rare but serious illness reported to be associated with aspirin.

Liver Warning:

This product contains Acetaminophen. Severe liver damage may occur if: ■ you take more than 8 tablets in 24 hours ■ you take with other drugs containing acetaminophen (prescription or non-prescription) ■ you have 3 or more alcoholic drinks every day while using this product.

Stomach Bleeding Warning:

This product contains a non-steroidal anti-inflammatory drug (NSAIDs), which may cause stomach bleeding. The chance is higher if you ■ have had stomach ulcers or bleeding problems ■ take a blood thinning (anticoagulant) or steroid drug ■ are age 60 or older ■ have 3 or more alcoholic drinks every day while using this product ■ take with other drugs containing a NSAID ■ you take more or for a longer time than directed.

Do not use:

■ if you are allergic to aspirin ■ with any other pain reliever/fever reducer ■ if you have ever had an allergic reaction to any other pain reliever/fever reducer ■ for pain for more than 10 days or for fever for more than 3 days unless directed by a doctor ■ with any other product containing acetaminophen

Ask doctor before using if you have:

■ asthma ■ stomach problems (such as heartburn, upset stomach or stomach pain) ■ gastric ulcers ■ bleeding problems

Ask a doctor or pharmacist before use if

you are taking a prescription drug for ■ anticoagulation (thinning of blood) ■ diabetes ■ gout ■ arthritis

Stop use and ask a doctor if

■ ringing in the ears or loss of hearing occurs • pain or fever persists or gets worse ■ new symptoms occur ■ redness or swelling is present

If pregnant or breast-feeding a baby,

ask a health professional before use. IT IS ESPECIALLY IMPORTANT NOT TO USE ASPIRIN DURING THE LAST 3 MONTHS OF PREGNANCY UNLESS SPECIFICALLY DIRECTED TO DO SO BY A DOCTOR BECAUSE IT MAY CAUSE PROBLEMS IN THE UNBORN CHILD OR COMPLICATIONS DURING DELIVERY.

KEEP OUT OF REACH OF CHILDREN.

In a case of overdose, get medical help or contact a Poison Control Center right away.

Prompt medical attention is critical for adults as well as for children even if you do not notice any signs or symptoms.

Directions:

Adults and children 12 years of age and older: Take 2 tablets every 4 hours as needed, with a full glass of water. Do not exceed 6 tablets in any 24 hour period
Children under 12 years: Ask a doctor

Other Information:

■ Tamper Evident. Do not use if packet is torn, cut or opened ■ Store at controlled room temperature 15˚ to 30˚C (59˚ to 86˚F) ■ Avoid excessive heat and humidity

Inactive Ingredients:

FD&C Yellow #6, magnesium stearate, microcrystalline cellulose, povidone, silicon dioxide, sodium starch glycolate, starch and stearic acid